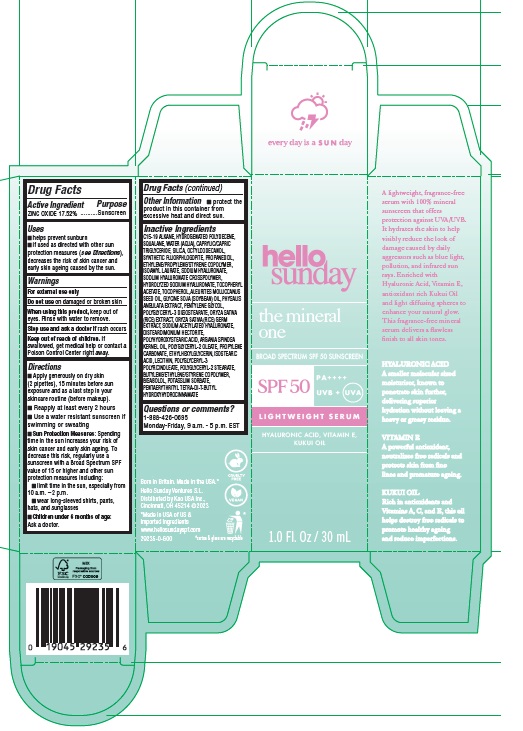 DRUG LABEL: Hello Sunday The Mineral One Lightweight Serum SPF 50
NDC: 10596-804 | Form: EMULSION
Manufacturer: Kao USA Inc.
Category: otc | Type: HUMAN OTC DRUG LABEL
Date: 20250131

ACTIVE INGREDIENTS: ZINC OXIDE 175.2 mg/1 mL
INACTIVE INGREDIENTS: ISOSTEARIC ACID; LECITHIN, SOYBEAN; PENTAERYTHRITOL TETRAKIS(3-(3,5-DI-TERT-BUTYL-4-HYDROXYPHENYL)PROPIONATE); POLYGLYCERYL-2 STEARATE; OCTYLDODECANOL; POLYGLYCERYL-3 PENTARICINOLEATE; POTASSIUM SORBATE; LEVOMENOL; C15-19 ALKANE; HYDROGENATED POLYDECENE (1500 CST); SQUALANE; WATER; MEDIUM-CHAIN TRIGLYCERIDES; SILICON DIOXIDE; MAGNESIUM POTASSIUM ALUMINOSILICATE FLUORIDE; PROPANEDIOL; ISOAMYL LAURATE; HYALURONATE SODIUM; .ALPHA.-TOCOPHEROL ACETATE; TOCOPHEROL; KUKUI NUT OIL; SOYBEAN OIL; PHYSALIS ANGULATA WHOLE; PENTYLENE GLYCOL; RICE GERM; SODIUM ACETYLATED HYALURONATE; DISTEARDIMONIUM HECTORITE; POLYHYDROXYSTEARIC ACID (2300 MW); ARGAN OIL; POLYGLYCERYL-3 DIISOSTEARATE; POLYGLYCERYL-2 OLEATE; PROPYLENE CARBONATE; ETHYLHEXYLGLYCERIN

Hello Sunday The Mineral One Lightweight Serum SPF 50

Active Ingredients

ZINC OXIDE 17.52%

Purpose

Sunscreen

Uses

- helps prevent sunburn
- if used as directed with other sun protection measures (see Directions), decreases the risk of skin cancer and early skin ageing caused by the sun.

Warnings

For external use only

Do not use

on damaged or broken skin

When using this product

keep out of eyes. Rinse with water to remove.

Stop use and ask a doctor if

rash occurs

Keep out of reach of children.

If swallowed, get medical help or contact a Poison Control Center right away.

Directions

- Apply generously on dry skin (2 pipettes), 15 minutes before sun exposure and as a last step in your skincare routine (before makeup).
- Reapply at least every 2 hours
- Use a water resistant sunscreen if swimming or sweating
- Sun Protection Measures: Spending time in the sun increases your risk of skin cancer and early skin ageing. To decrease this risk, regularly use a sunscreen with a Broad Spectrum SPF value of 15 or higher and other sun protection measures including:
- limit time in the sun, especially from 10 a.m. – 2 p.m.
- wear long-sleeved shirts, pants, hats, and sunglasses
- Children under 6 months of age: Ask a doctor.

Other Information

- protect the product in this container from excessive heat and direct sun.

Inactive Ingredients

C15-19 ALKANE, HYDROGENATED POLYDECENE, SQUALANE, WATER (AQUA), CAPRYLIC/CAPRIC TRIGLYCERIDE, SILICA, OCTYLDODECANOL, SYNTHETIC FLUORPHLOGOPITE, PROPANEDIOL, ETHYLENE/PROPYLENE/STYRENE COPOLYMER, ISOAMYL LAURATE, SODIUM HYALURONATE, SODIUM HYALURONATE CROSSPOLYMER, HYDROLYZED SODIUM HYALURONATE, TOCOPHERYL ACETATE, TOCOPHEROL, ALEURITES MOLUCCANUS SEED OIL, GLYCINE SOJA (SOYBEAN) OIL, PHYSALIS ANGULATA EXTRACT, PENTYLENE GLYCOL, POLYGLYCERYL-3 DIISOSTEARATE, ORYZA SATIVA (RICE) EXTRACT, ORYZA SATIVA (RICE) GERM EXTRACT, SODIUM ACETYLATED HYALURONATE, DISTEARDIMONIUM HECTORITE, POLYHYDROXYSTEARIC ACID, ARGANIA SPINOSA KERNEL OIL, POLYGLYCERYL-2 OLEATE, PROPYLENE CARBONATE, ETHYLHEXYLGLYCERIN, ISOSTEARIC ACID, LECITHIN, POLYGLYCERYL-3 POLYRICINOLEATE, POLYGLYCERYL-2 STEARATE,
BUTYLENE/ETHYLENE/STYRENE COPOLYMER, BISABOLOL, POTASSIUM SORBATE, PENTAERYTHRITYL TETRA-DI-T-BUTYL HYDROXYHYDROCINNAMATE

Questions or comments?

1-888-426-0695
Monday-Friday, 9 a.m. - 5 p.m. EST